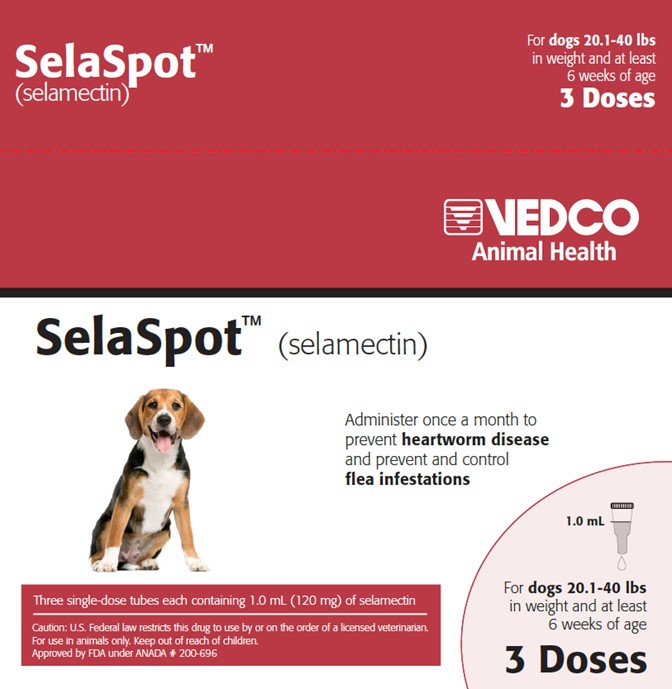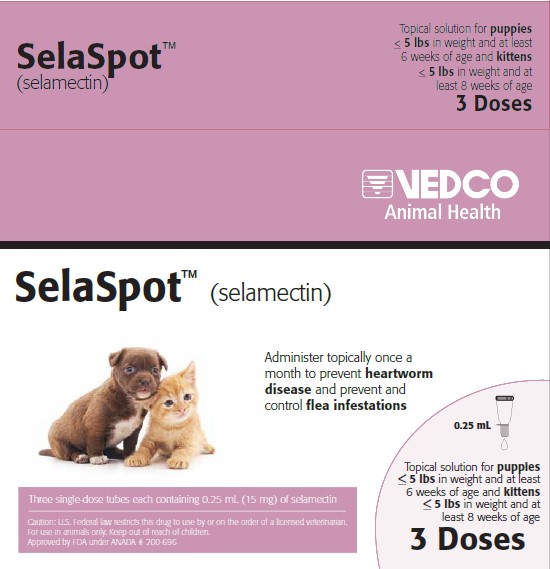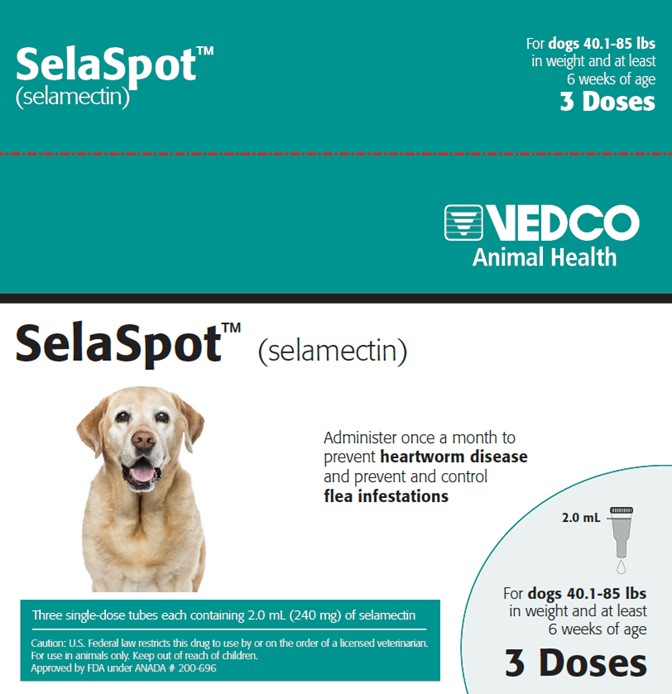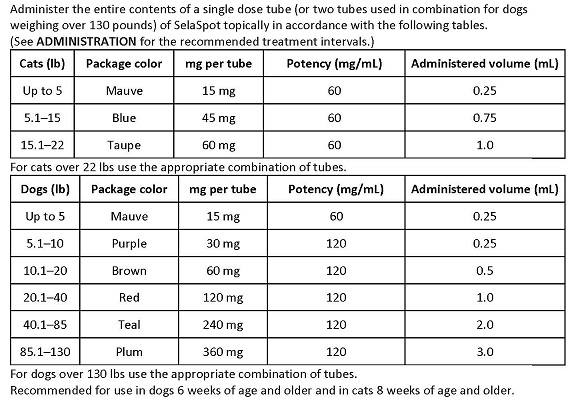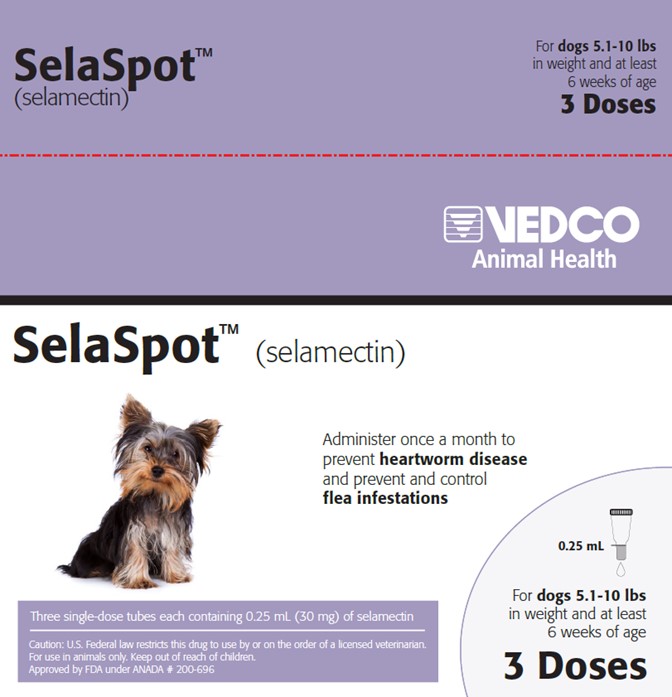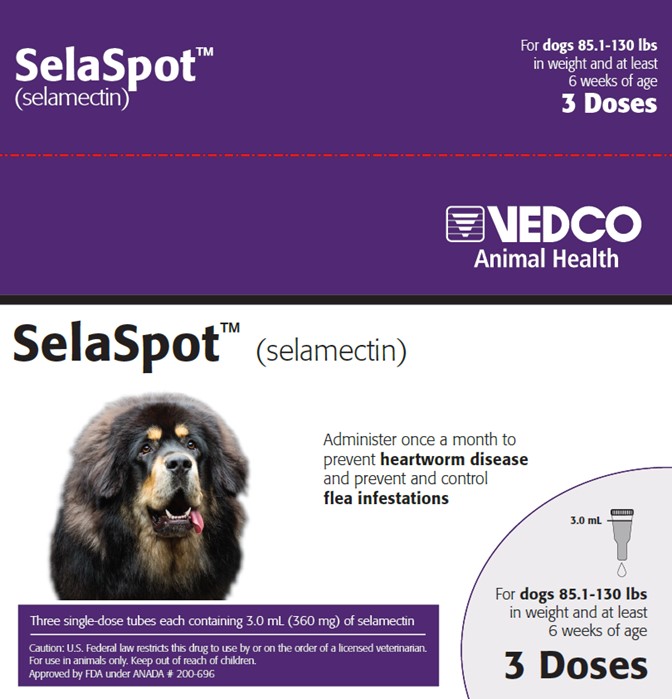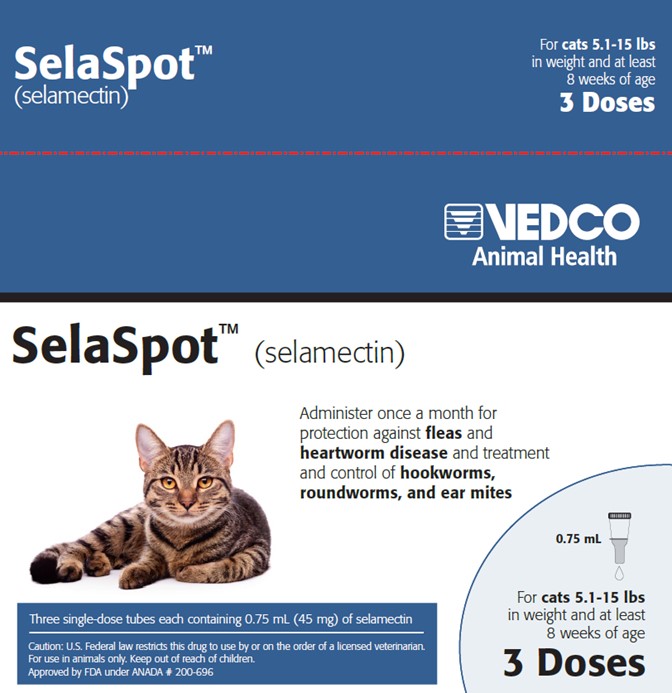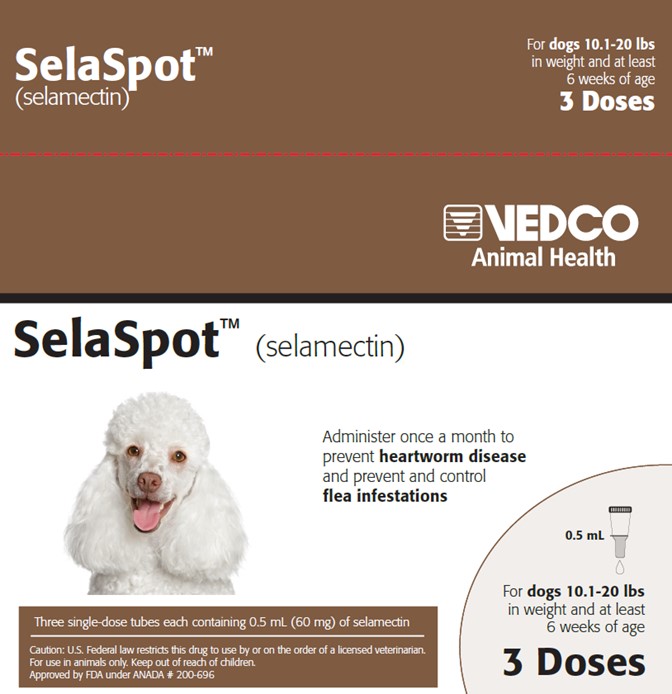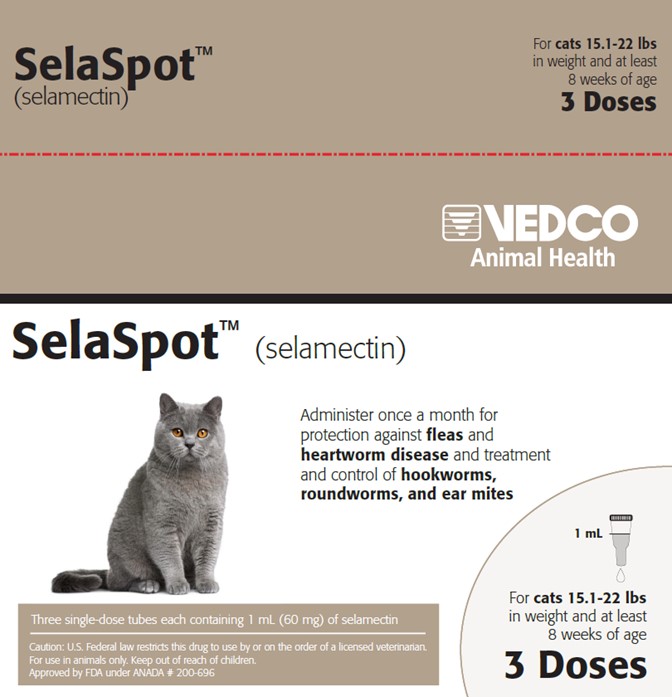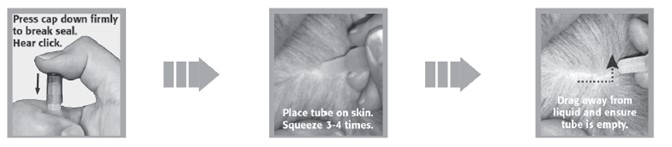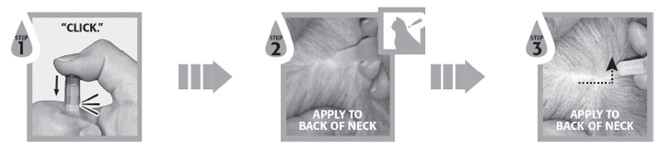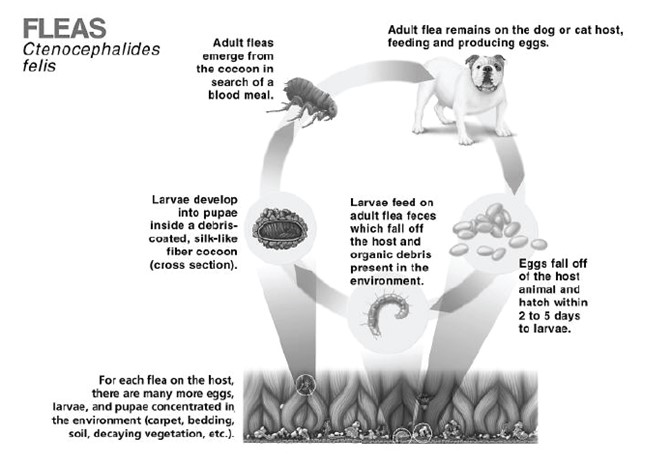 DRUG LABEL: SelaSpot
NDC: 50989-317 | Form: SOLUTION
Manufacturer: Vedco, Inc.
Category: animal | Type: PRESCRIPTION ANIMAL DRUG LABEL
Date: 20251229

ACTIVE INGREDIENTS: SELAMECTIN 60 mg/1 mL
INACTIVE INGREDIENTS: ISOPROPYL ALCOHOL; BUTYLATED HYDROXYTOLUENE

SelaSpot™ (selamectin)

SelaSpotTM (selamectin)
Topical Parasiticide For Dogs and Cats

CAUTION: US Federal law restricts this drug to use by or on the order of a licensed veterinarian.

DESCRIPTION:
SelaSpot (selamectin) Topical Parasiticide is available as a colorless to yellow, ready to use solution in single dose tubes for topical (dermal) treatment of dogs six weeks of age and older and cats eight weeks of age and older. The content of each tube is formulated to provide a minimum of 2.7 mg/lb (6 mg/kg) of body weight of selamectin. The chemical composition of selamectin is (5Z,25S)-25-cyclohexyl-4'-O-de(2,6-dideoxy-3-O-methyl-α-L-arabino-hexopyranosyl)-5-demethoxy-25-de(1-methylpropyl)-22,23-dihydro-5-hydroxyiminoavermectin A1a.

INDICATIONS:
SelaSpot is recommended for use in dogs six weeks of age or older and cats eight weeks of age and older for the following parasites and indications:

Dogs:
SelaSpot kills adult fleas and prevents flea eggs from hatching for one month and is indicated for the prevention and control of flea infestations (Ctenocephalides felis), prevention of heartworm disease caused by Dirofilaria immitis, and the treatment and control of ear mite (Otodectes cynotis) infestations. SelaSpot also is indicated for the treatment and control of sarcoptic mange (Sarcoptes scabiei) and for the control of tick infestations due to Dermacentor variabilis.

Cats:
SelaSpot kills adult fleas and prevents flea eggs from hatching for one month and is indicated for the prevention and control of flea infestations (Ctenocephalides felis), prevention of heartworm disease caused by Dirofilaria immitis, and the treatment and control of ear mite (Otodectes cynotis) infestations. SelaSpot is also indicated for the treatment and control of roundworm (Toxocara cati) and intestinal hookworm (Ancylostoma tubaeforme) infections in cats.

DOSAGE AND ADMINISTRATION:
The recommended minimum dose is 2.7 mg selamectin per pound (6 mg/kg) of body weight.

A veterinarian or veterinary technician should demonstrate or instruct the pet owner regarding the appropriate technique for applying SelaSpot topically to dogs and cats prior to first use.

Firmly press the cap down to puncture the seal on the SelaSpot tube; a clicking sound will confirm that the cap has successfully punctured the seal. Remove the cap and check to ensure that the tip of the tube is open. To administer the product, part the hair on the back of the animal at the base of the neck in front of the shoulder blades until the skin is visible. Place the tip of the tube on the skin and squeeze the tube 3 or 4 times to empty its entire contents directly onto the skin in one spot. Keeping the tube squeezed, drag it away from the liquid and lift to remove. Check the tube to ensure that it is empty. Do not massage the product into the skin. Due to alcohol content, do not apply to broken skin. Avoid contact between the product and fingers. Do not apply when the haircoat is wet. Bathing or shampooing the dog 2 or more hours after treatment will not reduce the effectiveness of SelaSpot against fleas or heartworm. Bathing or shampooing the cat 2 hours after treatment will not reduce the effectiveness of SelaSpot against fleas. Bathing or shampooing the cat 24 hours after treatment will not reduce the effectiveness of SelaSpot against heartworm. Stiff hair, clumping of hair, hair discoloration, or a slight powdery residue may be observed at the treatment site in some animals. These effects are temporary and do not affect the safety or effectiveness of the product. Discard empty tubes in your ordinary household refuse.

Flea Control in Dogs and Cats
For the prevention and control of flea infestations, SelaSpot should be administered at monthly intervals throughout the flea season, starting one month before fleas become active. In controlled laboratory studies >98% of fleas were killed within 36 hours. Results of clinical field studies using selamectin monthly demonstrated >90% control of flea infestations within 30 days of the first dose. Dogs and cats treated with selamectin, including those with pre-existing flea allergy dermatitis, showed improvement in clinical signs associated with fleas as a direct result of eliminating the fleas from the animals and their environment.
If the dog or cat is already infested with fleas when the first dose of SelaSpot is administered, adult fleas on the animal are killed and no viable fleas hatch from eggs after the first administration. However, an environmental infestation of fleas may persist for a short time after beginning treatment with SelaSpot because of the emergence of adult fleas from pupae.
Heartworm Prevention in Dogs and Cats
For the prevention of heartworm disease, SelaSpot must be administered on a monthly basis. SelaSpot may be administered year-round or at least within one month after the animal's first exposure to mosquitoes and monthly thereafter until the end of the mosquito season. The final dose must be given within one month after the last exposure to mosquitoes. If a dose is missed and a monthly interval between dosing is exceeded then immediate administration of SelaSpot and resumption of monthly dosing will minimize the opportunity for the development of adult heartworms. When replacing another heartworm preventive product in a heartworm disease prevention program, the first dose of SelaSpot must be given within a month of the last dose of the former medication.

Selamectin, the active ingredient in SelaSpot, is a macrocyclic lactone compound. These compounds effectively prevent the development of adult heartworms when administered to dogs and cats within one month of exposure to infective (L3) Dirofilaria immitis larvae. Efficacy of macrocyclic lactones decreases below 100% in dogs, however, if first administered >2 months after exposure to infective larvae. Thus, in heartworm endemic regions, delaying initiation of heartworm prevention using SelaSpot beyond 2 months of first exposure to infective larvae (e.g., starting puppies and kittens at >8 weeks of age), or gaps of >2 months in the administration of SelaSpot during periods of heartworm transmission, increases the risk of the animal acquiring heartworms. Animals with unknown heartworm history that test negative for heartworms prior to the initiation of SelaSpot may be harboring pre-patent infections at the time SelaSpot was started. Testing such animals 3–4 months after initiation of SelaSpot would be necessary to confirm their negative heartworm status.

At the discretion of the veterinarian, cats ≥6 months of age may be tested to determine the presence of existing heartworm infections before beginning treatment with SelaSpot. Cats already infected with adult heartworms can be given SelaSpot monthly to prevent further infections.

Ear Mite Treatment in Dogs and Cats
For the treatment of ear mite (O. cynotis) infestations in dogs and cats, SelaSpot should be administered once as a single topical dose. A second monthly dose may be required in some dogs. Monthly use of SelaSpot will control any subsequent ear mite infestations. In the clinical field trials ears were not cleaned, and many animals still had debris in their ears after the second dose. Cleansing of the infested ears is recommended to remove the debris.

Sarcoptic Mange Treatment in Dogs
For the treatment of sarcoptic mange (S. scabiei) in dogs, SelaSpot should be administered once as a single topical dose. A second monthly dose may be required in some dogs. Monthly use of SelaSpot will control any subsequent sarcoptic mange mite infestations. Because of the difficulty in finding sarcoptic mange mites on skin scrapings, effectiveness assessments also were based on resolution of clinical signs. Resolution of the pruritus associated with the mite infestations was observed in approximately 50% of the dogs 30 days after the first treatment and in approximately 90% of the dogs 30 days after the second monthly treatment.

Tick Control in Dogs
For the control of tick (Dermacentor variabilis) infestations in dogs, SelaSpot should be administered on a monthly basis. In heavy tick infestations, complete efficacy may not be achieved after the first dose. In these cases, one additional dose may be administered two weeks after the previous dose, with monthly dosing continued thereafter.

Nematode Treatment in Cats
For the treatment and control of intestinal hookworm (A. tubaeforme) and roundworm (T. cati) infections, SelaSpot should be applied once as a single topical dose.

WARNINGS:
User Safety Warnings
Not for human use. Keep out of the reach of children.
In humans, SelaSpot may be irritating to skin and eyes.
Reactions such as hives, itching and skin redness have been reported in humans. Individuals with known hypersensitivity to SelaSpot should use the product with caution or consult a health care professional. SelaSpot contains isopropyl alcohol and the preservative butylated hydroxytoluene (BHT). Wash hands after use and wash off any product in contact with the skin immediately with soap and water. If contact with eyes occurs, then flush eyes copiously with water; if wearing contact lenses, rinse the eyes first then remove contact lenses and continue to rinse for 5-10 minutes and seek medical attention.
In case of ingestion by a human, contact a physician immediately.
The safety data sheet (SDS) provides more detailed occupational safety information. To obtain a SDS contact Bimeda, Inc. at 1-888-524-6332 or www.bimeda.com.

Flammable - Keep away from heat, sparks, open flames or other sources of ignition.

Animal Safety Warnings
Do not use in sick, debilitated or underweight animals (see TARGET ANIMAL SAFETY).

PRECAUTIONS:
Prior to administration of SelaSpot, dogs should be tested for existing heartworm infections. At the discretion of the veterinarian, infected dogs should be treated to remove adult heartworms. SelaSpot is not effective against adult D. immitis and, while the number of circulating microfilariae may decrease following treatment, SelaSpot is not effective for microfilariae clearance.

Hypersensitivity reactions have not been observed in dogs with patent heartworm infections administered selamectin (see TARGET ANIMAL SAFETY).

ADVERSE REACTIONS:

Pre-Approval Clinical Trials:

Following treatment with selamectin, transient localized alopecia with or without inflammation at or near the site of application was observed in approximately 1% of 691 treated cats. Other signs observed (≤0.5% of 1743 treated cats and dogs) included vomiting, loose stool or diarrhea with or without blood, anorexia, lethargy, salivation, tachypnea, and muscle tremors.

Post-Approval Experience (2021):

The following adverse events are based on post-approval adverse drug experience reporting for selamectin. Not all adverse events are reported to FDA/CVM. It is not always possible to reliably estimate the adverse event frequency or establish a causal relationship to product exposure using this data.

The following adverse events reported for dogs are listed in decreasing order of reporting frequency:
Lethargy, vomiting, diarrhea, anorexia, generalized pruritus, seizures, application site reactions (including alopecia, lesions, erythema, pruritis, and inflammation), tremors, ataxia, death, and dermatitis.

The following adverse events reported for cats are listed in decreasing order of reporting frequency:
Application site reactions (including alopecia, lesions, erythema, pruritis, inflammation, vesicles, blisters, and excoriations), lethargy, anorexia, vomiting, death, generalized pruritis, diarrhea, ataxia, fever, generalized alopecia, tremors, hypersalivation, dermatitis, and seizures.

CONTACT INFORMATION:
Contact Bimeda, Inc. at 1-888-524-6332 or www.bimeda.com. To report suspected drug experiences, contact Bimeda, Inc. at 1-888-534-6332. For additional information about reporting adverse drug experiences for animal drugs, contact FDA at 1-888-FDA-VETS or www.fda.gov/reportanimalae.

TARGET ANIMAL SAFETY:
Selamectin has been tested safe in over 100 different pure and mixed breeds of healthy dogs and over 15 different pure and mixed breeds of healthy cats, including pregnant and lactating females, breeding males and females, puppies six weeks of age and older, kittens eight weeks of age and older, and avermectin-sensitive collies. A kitten, estimated to be 5–6 weeks old (0.3 kg), died 8 1⁄2 hours after receiving a single treatment of selamectin at the recommended dosage. The kitten displayed clinical signs which included muscle spasms, salivation and neurological signs. The kitten was a stray with an unknown history and was malnourished and underweight (see WARNINGS).

DOGS: In safety studies, selamectin was administered at 1, 3, 5, and 10 times the recommended dose to six-week-old puppies, and no adverse reactions were observed. The safety of selamectin administered orally also was tested in case of accidental oral ingestion. Oral administration of selamectin at the recommended topical dose in 5- to 8-month-old beagles did not cause any adverse reactions. In a pre-clinical study selamectin was dosed orally to ivermectin-sensitive collies. Oral administration of 2.5, 10, and 15 mg/kg in this dose escalating study did not cause any adverse reactions; however, eight hours after receiving 5 mg/kg orally, one avermectin-sensitive collie became ataxic for several hours, but did not show any other adverse reactions after receiving subsequent doses of 10 and 15 mg/kg orally. In a topical safety study conducted with avermectin-sensitive collies at 1, 3 and 5 times the recommended dose of selamectin, salivation was observed in all treatment groups, including the vehicle control. Selamectin also was administered at 3 times the recommended dose to heartworm infected dogs, and no adverse effects were observed.

CATS: In safety studies, selamectin was applied at 1, 3, 5, and 10 times the recommended dose to six-week-old kittens. No adverse reactions were observed. The safety of selamectin administered orally also was tested in case of accidental oral ingestion. Oral administration of the recommended topical dose of selamectin to cats caused salivation and intermittent vomiting. Selamectin also was applied at 4 times the recommended dose to patent heartworm infected cats, and no adverse reactions were observed.
In well-controlled clinical studies, selamectin was used safely in animals receiving other frequently used veterinary products such as vaccines, anthelmintics, antiparasitics, antibiotics, steroids, collars, shampoos and dips.

STORAGE CONDITIONS: Store below 25°C (77°F).

HOW SUPPLIED

HOW SUPPLIED: Available in eight separate dose strengths for dogs and cats of different weights (see DOSAGE). SelaSpot for puppies and kittens is available in cartons containing 3 single dose tubes. SelaSpot for cats and dogs is available in cartons containing 3 single dose tubes.

Approved by FDA under ANADA # 200-696

Manufactured by: | Manufactured for:
Bimeda, Inc. | VEDCO, Inc
Le Sueur, MN 56058 | St. Joseph, MO 64507

www.bimeda.com

Client Information About

SelaSpotTM (selamectin)

SelaSpot (pronounced “Sel-a-Spot”)
Generic name: selamectin ("sel-a-mec-tin")

This summary contains important information about SelaSpot. You should read this information before you start using SelaSpot on your dog or cat and review it each time your prescription is refilled. This sheet is provided only as a summary and does not take the place of instructions from your veterinarian. Talk to your veterinarian if you do not understand any of this information or if you want to know more about SelaSpot.

What is SelaSpot?
SelaSpot is a topical parasiticide that is applied to the skin of dogs six weeks of age and older and cats eight weeks of age and older to kill adult fleas and prevent flea eggs from hatching, prevent heartworm disease and protect your pet against other parasites (see below).

Why has my veterinarian prescribed SelaSpot?
SelaSpot has been prescribed by your veterinarian to treat, prevent and/or control the following parasites in your dog or cat:

Dog Parasites:

- Control and prevention of flea infestation (Ctenocephalides felis)
- Prevention of heartworm disease (Dirofilaria immitis)
- Treatment and control of ear mite infestation (Otodectes cynotis)
- Treatment and control of sarcoptic mange (Sarcoptes scabiei)
- Control of the American Dog Tick (Dermacentor variabilis)

Cat Parasites:

- Control and prevention of flea infestation (Ctenocephalides felis)
- Prevention of heartworm disease (Dirofilaria immitis)
- Treatment and control of ear mite infestation (Otodectes cynotis)
- Treatment and control of intestinal worms

Roundworm (Toxocara cati)
Hookworm (Ancylostoma tubaeforme)

What should I discuss with my veterinarian before SelaSpot is prescribed?
Your veterinarian is best suited to discuss and recommend appropriate medications for your dog or cat. It is important to discuss your pet's health history with your veterinarian so he/she can decide if SelaSpot is right for your animal.

SelaSpot should not be used in sick, debilitated or underweight animals.
Dogs should be tested for heartworm disease prior to giving SelaSpot. If your dog tests positive for adult heartworms, your veterinarian can recommend appropriate treatment. Dogs infected with adult heartworms can safely be given SelaSpot.
If your cat is older than six months of age, your veterinarian may decide to test him/her for heartworm disease before prescribing SelaSpot. Cats infected with adult heartworms can be given SelaSpot to prevent further infections.

What dose of SelaSpot do I use on my dog or cat?
Your veterinarian will recommend the appropriate dose for your dog or cat based on your animal's body weight. You should not administer SelaSpot to dogs younger than 6 weeks of age or cats younger than 8 weeks of age. SelaSpot is available in eight separate dose strengths for dogs and cats of different weights.

What should I do if I do not give SelaSpot on time or miss a dose?
If you forget to apply a monthly dose of SelaSpot immediately apply SelaSpot, resume monthly applications, and notify your veterinarian.

What if I administer more than the prescribed amount of SelaSpot to my dog or cat?
Contact your veterinarian if you administer more than the prescribed amount of SelaSpot.

How should SelaSpot be applied?

1. Remove the SelaSpot tube from its protective package.

2. Holding the tube upright, firmly press the cap down until you hear a 'click' sound, which signals that the cap has punctured the applicator seal. Remove the cap and check to be sure that the tip of the tube is open.

3. Part the hair on the back of the animal at the base of the neck, in front of the shoulder blades, until the skin is visible.

4. Apply the tip of the SelaSpot tube directly to the skin. Squeeze the tube firmly 3–4 times in one spot until empty. Keep tube compressed on the final squeeze to avoid drawing liquid back into tube. Avoid contact between SelaSpot and your fingers.

5. While keeping tube squeezed, drag it away from liquid and lift up to remove.

6. Ensure tube is empty.

Do not massage SelaSpot into the skin.
Do not apply when the haircoat is wet.
Do not apply to broken skin – SelaSpot contains alcohol.

Stiff hair, clumping of hair, hair discoloration, or a slight powdery residue may be observed at the site in some animals. These effects are usually temporary and do not affect the safety or effectiveness of the product.

Can I give my pet a bath after applying SelaSpot?
Yes. Bathing or shampooing the dog 2 or more hours after treatment will not reduce the effectiveness of SelaSpot against fleas or heartworm. Bathing or shampooing the cat 24 hours after treatment will not reduce the effectiveness of SelaSpot against fleas or heartworm.

When can I play with my pet following treatment with SelaSpot?
You should avoid contact with application site when wet. You may hold or play with your pet any time after the area on which SelaSpot was applied is dry.

I see fleas on my dog or cat. Is SelaSpot working?
SelaSpot kills adult fleas and prevents flea eggs from hatching. You may occasionally see a few fleas on dogs or cats treated with SelaSpot but more than 98% of adult fleas are killed within 36 hours.
Immature stages of the flea called pupae may be present in your pets' environment (yard, flooring, carpet, bedding, etc.). These pupae are not killed by parasiticides (including SelaSpot) and as such may emerge as adult fleas. These adult fleas may hop onto your pet at anytime. They must be exposed to SelaSpot on your dog or cat before being killed. It can take from 3–5 weeks (or longer depending on environmental conditions) for most fleas to complete their 4-stage life cycle (egg, larvae, pupae, and adult) and reach the adult stage before being seen on your pet. Due to the presence of immature flea stages in infested environments it can take up to 2 to 3 monthly applications for SelaSpot to maximally control the infestation of fleas in the environment. Once the flea population is controlled you will be less likely to see fleas.

I see ticks on my dog. Is SelaSpot working?

SelaSpot controls tick infestations only due to the American Dog Tick (Dermacentor variabilis), a tick commonly found on dogs. There are other common species of ticks that are not killed or controlled by SelaSpot. Your veterinarian can recommend appropriate products to control or kill ticks common to your area. For the control of the American Dog Tick, SelaSpot should be applied once a month; however, your veterinarian may recommend a second administration applied 14 days after the first dose if your dog has a heavy tick infestation and/or recommend additional tick control methods. It may take up to 5 days to kill the majority of ticks on your dog.

What are the possible side effects of SelaSpot?
Following the use of selamectin, the following side effects have been seen, listed in decreasing order of frequency for each species.
Dogs- Sluggishness, vomiting, diarrhea (with or without blood), decreased appetite, generalized itching, seizures, hair loss or skin redness at the application site, trembling, incoordination, skin inflammation, drooling, and rapid breathing.
In some cases, death has been reported in dogs.
Cats- Hair loss at the site of application with or without redness, flaking, or itching, sluggishness, decreased appetite, vomiting, generalized itching, diarrhea (with or without blood), incoordination, fever, hair loss, trembling, drooling, skin inflammation, and seizures.
Severe application site reactions like blisters, scabbing, and infection have been reported in cats.
In some cases, death has been reported in cats.

Can SelaSpot be given with other medicines?
In well-controlled clinical studies, selamectin was used safely in dogs and cats receiving other veterinary products such as vaccines, anthelmintics, antiparasitics, antibiotics, steroids, collars, shampoos and dips.
Tell your veterinarian about all medicines you have given your dog or cat in the past, and any medicines that you are planning to use with SelaSpot. This should include other medicines that you can get without a prescription. Your veterinarian may want to check that all of your dog's or cat's medicines can be given together.

How should SelaSpot be stored?
SelaSpot is flammable – Keep away from heat, sparks, open flames or other sources of ignition. Store below 25°C (77°F). After application, empty tubes can be placed in your normal household refuse for disposal.

What else should I know about SelaSpot?
SelaSpot is not for use in humans.
SelaSpot should be kept out of reach of children.
In humans, SelaSpot may be irritating to skin and eyes. Reactions such as hives, itching and skin redness have been reported in humans. Individuals with known hypersensitivity to SelaSpot should use the product with caution or consult a health care professional.
SelaSpot contains isopropyl alcohol and the preservative butylated hydroxytoluene (BHT).
Wash hands after use and wash off any product in contact with skin immediately with soap and water. In case of human ingestion contact a doctor immediately.

Approved by FDA under ANADA # 200-696